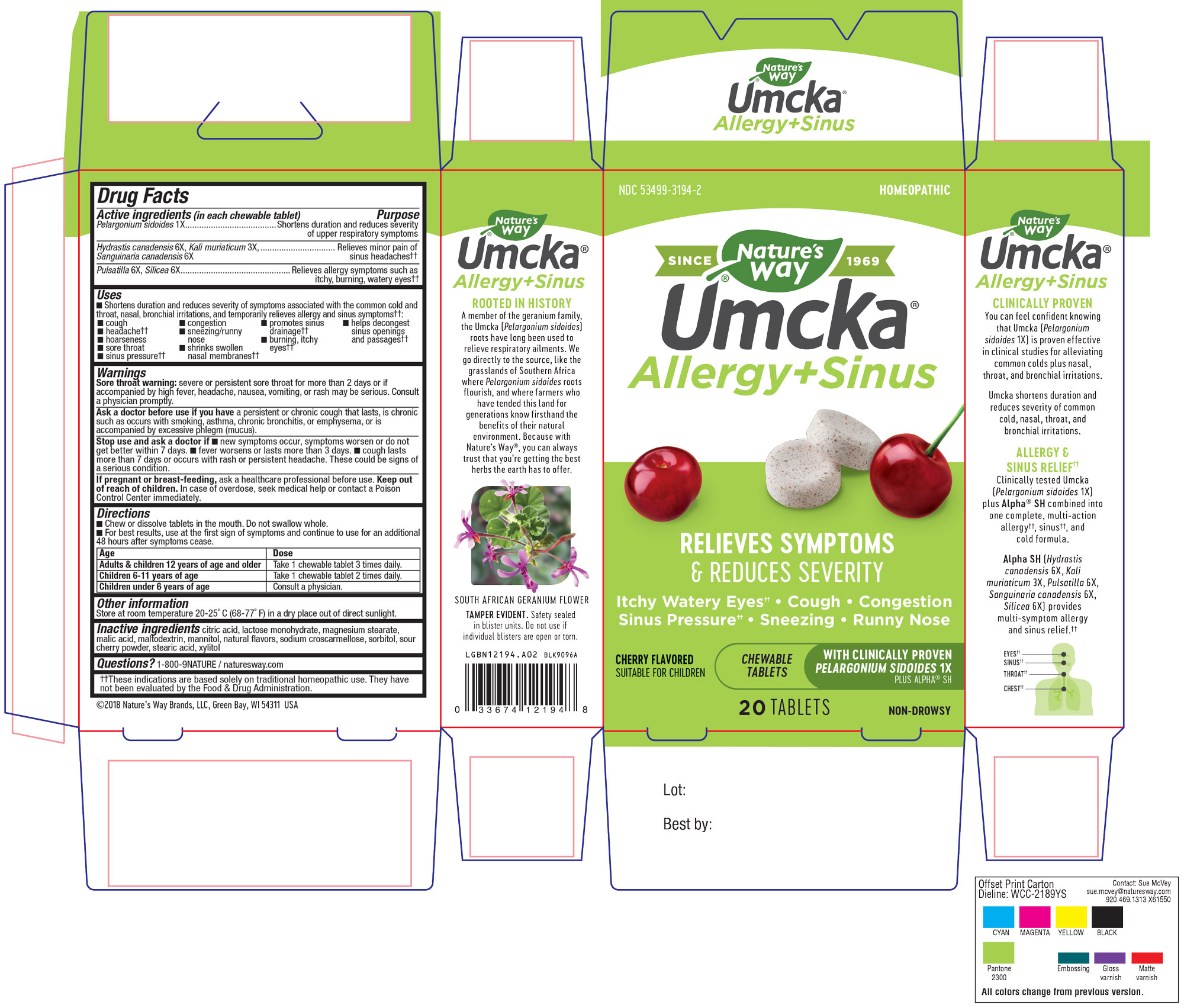 DRUG LABEL: Umcka Allergy and Sinus
NDC: 53499-3194 | Form: TABLET, CHEWABLE
Manufacturer: Schwabe North American, Inc.
Category: homeopathic | Type: HUMAN OTC DRUG LABEL
Date: 20241025

ACTIVE INGREDIENTS: PELARGONIUM SIDOIDES ROOT 1 [hp_X]/1 1; HYDRASTIS CANADENSIS WHOLE 6 [hp_X]/1 1; POTASSIUM CHLORIDE 3 [hp_X]/1 1; SANGUINARIA CANADENSIS ROOT 6 [hp_X]/1 1; PULSATILLA VULGARIS 6 [hp_X]/1 1; SILICON DIOXIDE 6 [hp_X]/1 1
INACTIVE INGREDIENTS: CHERRY; CITRIC ACID MONOHYDRATE; LACTOSE MONOHYDRATE; MAGNESIUM STEARATE; MALIC ACID; MALTODEXTRIN; MANNITOL; CROSCARMELLOSE SODIUM; SORBITOL; STEARIC ACID; XYLITOL

Umcka Allergy and Sinus

Active Ingredient

Pelargonium sidoides 1X

Hydrastis canadensis 6X

Kali muriaticum 3X

Sanguinaria canadensis 6X

Pulsatilla 6X

Silicea 6X

Inactive Ingredient

Citric Acid

Lactose Monohydrate

Magnesium Sterate

Malic Acid

Maltodextrin

Mannitol

Natural Flavors

Sodium Croscarmellose

Sorbitol

Sour Cherry Powder

Stearic acid

Xylitol

Purpose

Shortens duration and reduces severity of symptoms associated with the common cold and throat, nasal, bronchial irritations and temporarily relieves allergy and sinus symptoms: cough, congestion, promotes sinus drainage, helps decongest sinus openings and passages, headache, sneezing/runny nose, burning, itchy eyes, sore throat, shrinks swollen nasal membranes, sinus presssure.

Indications & Usage

Shortens duration and reduces severity of symptoms associated with the common cold and throat, nasal, bronchial irritations and temporarily relieves allergy and sinus symptoms: cough, congestion, promotes sinus drainage, helps decongest sinus openings and passages, headache, sneezing/runny nose, burning, itchy eyes, sore throat, shrinks swollen nasal membranes, sinus presssure.

Dosage & Administration

Firections

Chew or dissolve tablets in mouth. Do not swallow whole. For best results, use at first sign of symptoms and continue to use for an additional 48 hours after symptoms cease.

Adults & Children 12 years of age and older: Take 1 chewable tablet 3 times daily.

Children 6-11 of age: Take 1 chewable tablet 2 times daily.

Children under 6 years of age: Consult a physician

Warnings

Sore throat warning: severe or persistent sore throat for more than 2 days or if accompanied by high fever, headache, nausea, vomiting, or rash may be serious.

Consult a physician promptly.

Ask Doctor

Ask a doctor before use if you have a persistant or chronic cough that lasts, is chronic such as ocurs with smoking, asthma, chronic bronchitis, or emphysema, or is accompanied by excessive phlegm (mucus).

Stop Use

Stop use and ask a doctor if new symptoms occur, symptoms worsen or do not get better within 7 days, fever worsens or lasts more than 3 days, cough lasts more than 7 days or occurs with rash or persistent headache.

These could be signs of a serious condition.

Pregnancy or Breast Feeding

If pregnant or breast-feeding, ask a healthcare professional before use.

Keep out of reach of children

Overdose

In case of Overdose, seek medical help or contact a Poison Control center immediately.

PACKAGE LABEL

Add image transcription here...